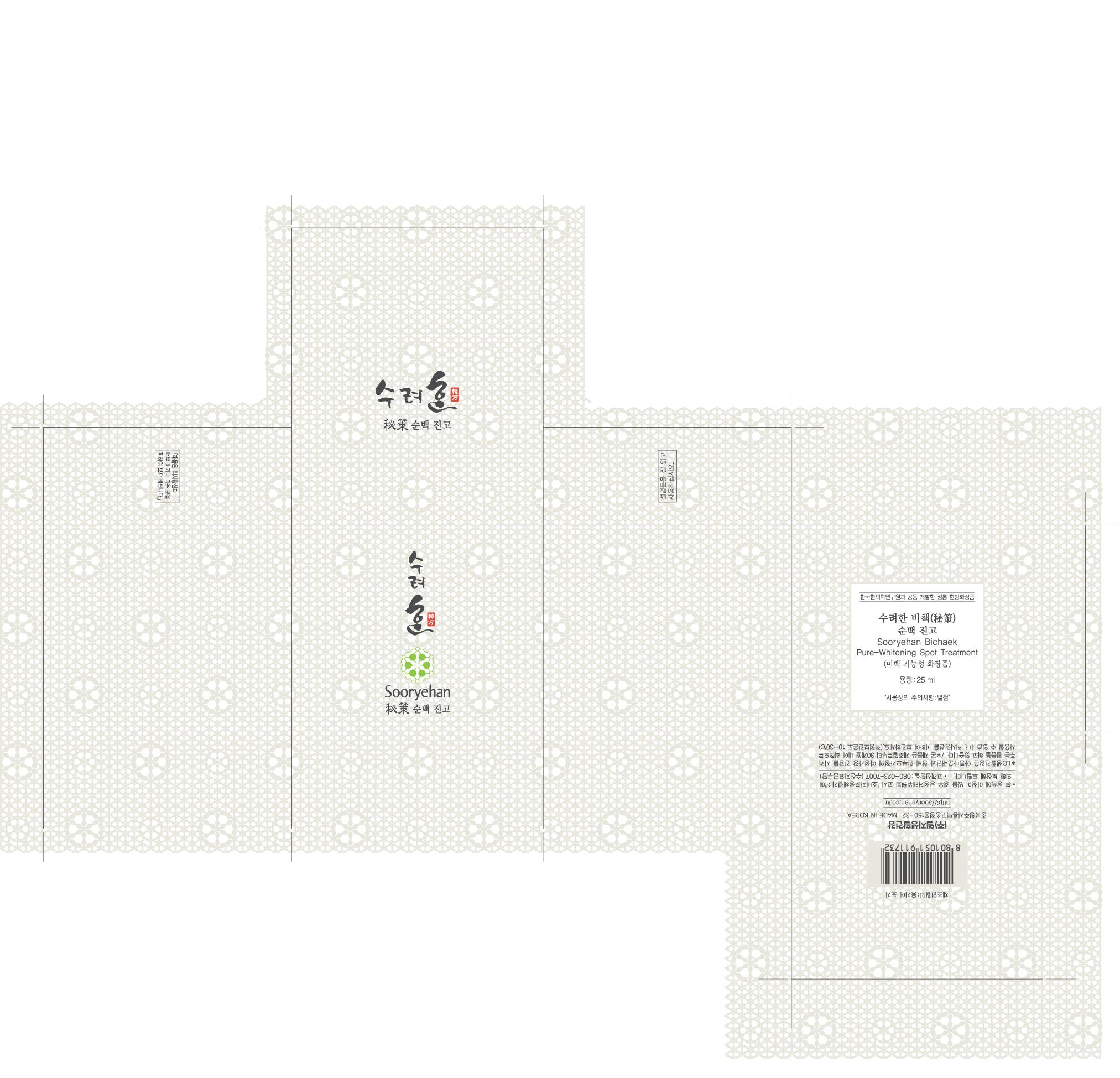 DRUG LABEL: Sooryehan Pure Whitening Spot Treatment
NDC: 53208-444 | Form: CREAM
Manufacturer: LG Household and Healthcare, Inc.
Category: otc | Type: HUMAN OTC DRUG LABEL
Date: 20100503

ACTIVE INGREDIENTS: POLYDATIN 0.21 mL/100 mL
INACTIVE INGREDIENTS: WATER; GLYCERIN; DIPROPYLENE GLYCOL; CAPRYLIC/CAPRIC MONO/DIGLYCERIDES; DIMETHICONE; CYCLOMETHICONE 5; CETOSTEARYL ALCOHOL; GLYCERYL MONOSTEARATE; PANTHENOL; TITANIUM DIOXIDE; TROLAMINE; FD&C YELLOW NO. 5; FD&C YELLOW NO. 6

DRUG FACTS

ACTIVE INGREDIENT

POLYDATIN 0.21mL/100mL

WARNINGS AND PRECAUTIONS

For external use only

Keep out of reach of children. Is swallowed, get medical help or contact a Poison Control Center right away.

WHEN USING

Keep out of eyes. Rinse with water to remove.

Stop use if a rash or irritation develops and lasts.